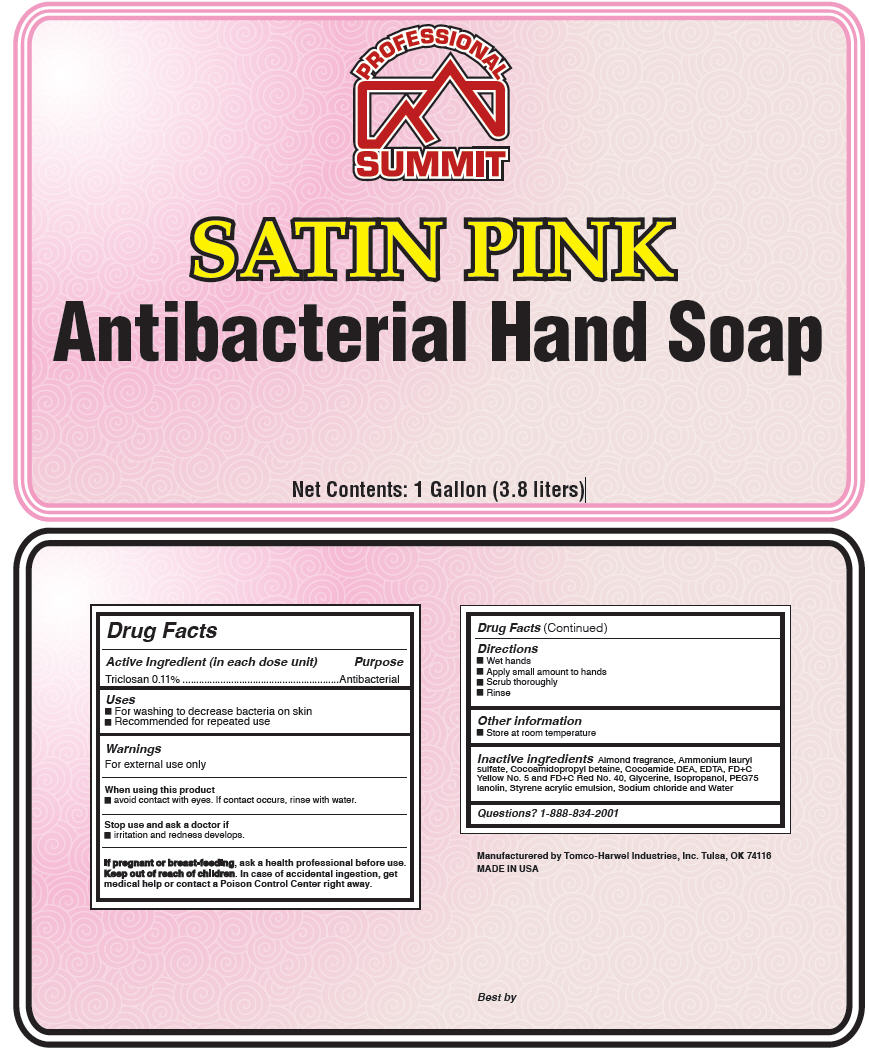 DRUG LABEL: Satin Pink
NDC: 60549-2108 | Form: LIQUID
Manufacturer: Tomco-Harwel Industries Inc
Category: otc | Type: HUMAN OTC DRUG LABEL
Date: 20140415

ACTIVE INGREDIENTS: Triclosan 1.08 g/1 L
INACTIVE INGREDIENTS: Water; EDETATE SODIUM; AMMONIUM LAURYL SULFATE; LANOLIN; GLYCERIN; ISOPROPYL ALCOHOL; COCAMIDOPROPYL BETAINE; COCO DIETHANOLAMIDE; SODIUM CHLORIDE; FD&C YELLOW NO. 5; FD&C RED NO. 40

Satin Pink

Drug Facts

Active Ingredient (in each dose unit)

Triclosan 0.11%

Purpose

Antibacterial

Uses

- For washing to decrease bacteria on skin
- Recommended for repeated use

Warnings

For external use only

When using this product

- avoid contact with eyes. If contact occurs, rinse with water.

Stop use and ask a doctor if

- irritation and redness develops.

PREGNANCY OR BREAST FEEDING

If pregnant or breast-feeding, ask a health professional before use.

Keep out of reach of children. In case of accidental ingestion, get medical help or contact a Poison Control Center right away.

Directions

- Wet hands
- Apply small amount to hands
- Scrub thoroughly
- Rinse

Other information

- Store at room temperature

Inactive ingredients

Almond fragrance, Ammonium lauryl sulfate, Cocoamidopropyl betaine, Cocoamide DEA, EDTA, FD+C Yellow No. 5 and FD+C Red No. 40, Glycerine, Isopropanol, PEG75 lanolin, Styrene acrylic emulsion, Sodium chloride and Water

Questions?

1-888-834-2001

Manufacturered by Tomco-Harwel Industries, Inc. Tulsa, OK 74116

PRINCIPAL DISPLAY PANEL - 3.8 Liter Bottle Label

PROFESSIONAL
SUMMIT

SATIN PINK
Antibacterial Hand Soap

Net Contents: 1 Gallon (3.8 liters)